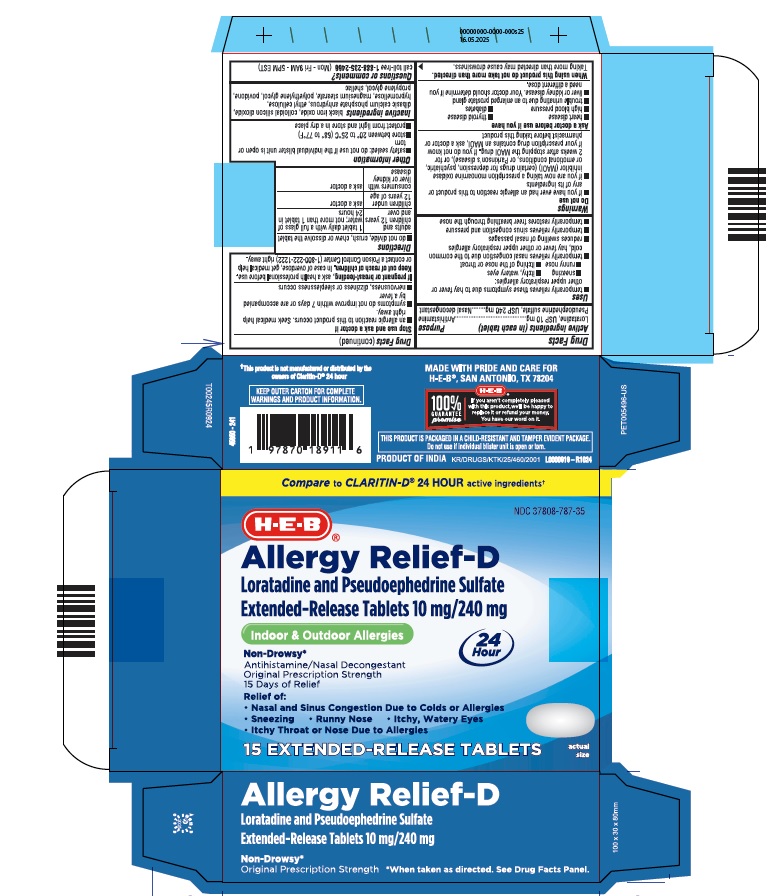 DRUG LABEL: Allergy Relief-D
NDC: 37808-787 | Form: TABLET, EXTENDED RELEASE
Manufacturer: HEB
Category: otc | Type: HUMAN OTC DRUG LABEL
Date: 20250527

ACTIVE INGREDIENTS: PSEUDOEPHEDRINE SULFATE 240 mg/1 1; LORATADINE 10 mg/1 1
INACTIVE INGREDIENTS: FERROSOFERRIC OXIDE; SILICON DIOXIDE; CALCIUM PHOSPHATE, DIBASIC, ANHYDROUS; ETHYLCELLULOSES; HYPROMELLOSES; MAGNESIUM STEARATE; POLYETHYLENE GLYCOL, UNSPECIFIED; POVIDONE; PROPYLENE GLYCOL; SHELLAC

HEB-Loratadine and Pseudoephedrine sulfate ER tablets

Active ingredient (in each capsule)

Loratadine, USP 10 mg

Pseudoephedrine sulfate, USP 240 mg

Purpose

Antihistamine

Nasal decongestant

Uses

• temporarily relieves these symptoms due to hay fever or other upper respiratory allergies:

• sneezing •itchy, watery eyes

• runny nose • itching of the nose or throat

• temporarily relieves nasal congestion due to the common cold, hay fever or other upper respiratory allergies

• reduces swelling of nasal passages

• temporarily relieves sinus congestion and pressure

• temporarily restores freer breathing through the nose

Warnings

Do not use

• if you have ever had an allergic reaction to this product or any of its ingredients.

• if you are now taking a prescription monoamine oxidase inhibitor (MAOI) (certain drugs for depression, psychiatric, or emotional conditions, or Parkinson's disease), or for 2 weeks after stopping the MAOI drug. If you do not know if your prescription drug contains an MAOI, ask a doctor or pharmacist before taking this product

Ask a doctor before use if you have

• heart disease • thyroid disease

• high blood pressure • diabetes

• trouble urinating due to enlarged prostrate gland

• liver or kidney disease. Your doctor should determine if you need a different dose.

When using this product

do not take more than directed. Taking more than directed may cause drowsiness.

Stop use and ask a doctor if

• an allergic reaction to this product occurs. Seek medical help right away.

• symptoms do not improve within 7 days or are accompanied by a fever

• nervousness, dizziness or sleeplessness occurs

If pregnant or breast-feeding,

ask a health professional before use.

Keep out of reach of children.

In case of overdose, get medical help or contact a Poison Control Center (1-800-222-1222) right away.

Directions

• do not divide, crush, chew or dissolve the tablet

adults and children 12 years and over | 1 tablet daily with a full glass of water; not more than 1 tablet in 24 hours
children under 12 years of age | ask a doctor
consumers with liver or kidney disease | ask a doctor

Other information

- Safety sealed: do not use if individual blister unit is open or torn
- store between 20° to 25°C (68° to 77°F)
- protect from light and store in a dry place

Inactive ingredients

black iron oxide, colloidal silicon dioxide, dibasic calcium phosphate anhydrous, ethyl cellulose, hypromellose, magnesium stearate, polyethylene glycol, povidone, propylene glycol, shellac

Questions or comments?

call toll free 1-888-235-2466 (Mon - Fri 9AM - 5PM EST)

KEEP OUTER CARTON FOR COMPLETE

WARNINGS AND PRODUCT INFORMATION

THIS PRODUCT IS PACKAGED IN A CHILD-RESITANT AND TAMPER EVIDENT PACKAGE.

Do not use if individual blister unit is open or torn.

†This product is not manufactured or distributed by the

owners of Claritin-D® 24 hour

MADE WITH PRIDE AND CARE FOR

H-E-B® , SAN ANTONIO, TX 78204

100%

GUARANTEE

promise

If you aren't completely pleased

with this product, we'll be happy to

replace it or refund your money.

You have our word on it.

PRODUCT OF INDIA

L0000918-R1024

KD/DRUGS/KTK/25/460/2001

15's carton

Compare to CLARITIN-D® 24 HOUR active ingredients ƚ

NDC 37808-787-35

H.E.B

Allergy Relief-D

Loratadine and Pseudoephedrine Sulfate

Exrended-Release Tablets 10 mg/ 240 mg

Indoor & Outdoor Allergies

24

Hour

Non-Drowsy*

Antihistamine/Nasal Decongestant

Original Prescription Strength

15 days of Relief

Relief of:

• Nasal and Sinus Congestion Due to Colds or Allergies

• Sneexing • Runny Nose • Itchy, Watery Eyes

• Itchy Throat or Nose Due to Allergies

15 EXTENDED- RELEASE TABLETS